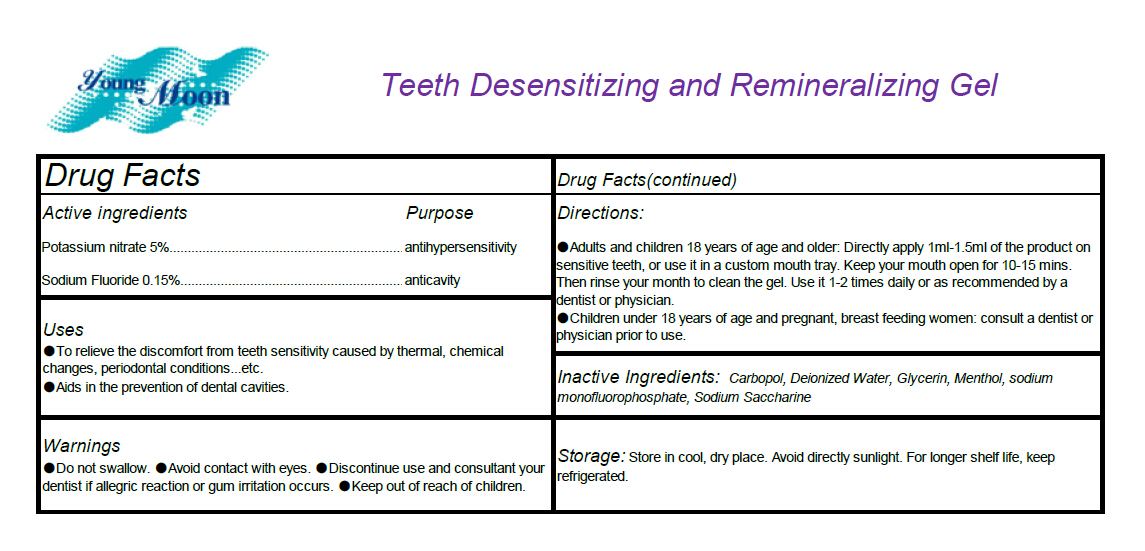 DRUG LABEL: teeth desensitizing and remineralizing gel
NDC: 49410-200 | Form: PASTE
Manufacturer: Fuzhou Difeng Bio-tech Co., Ltd.
Category: otc | Type: HUMAN OTC DRUG LABEL
Date: 20180106

ACTIVE INGREDIENTS: POTASSIUM NITRATE 50 mg/1 g; SODIUM FLUORIDE 1.5 mg/1 g
INACTIVE INGREDIENTS: SODIUM MONOFLUOROPHOSPHATE; MENTHOL; GLYCERIN; WATER; SACCHARIN SODIUM; CARBOMER HOMOPOLYMER TYPE A

teeth desensitizing and remineralizing gel 49410-200

Active ingredients

Potassium nitrate 5%
Sodium Fluoride 0.15%

Purpose

.antihypersensitivity
.anticavity

Uses

To relieve the discomfort from teeth sensitivity caused by thermal, chemical changes, periodontal
conditions...etc. Aids in the prevention of dental cavities.

Warnings

Do not swallow. Avoid contact with eyes. Discontinue use and consultant your dentist if allegric
reaction or gum irritation occurs.

Keep out of reach of children.

Directions

Adults and children 18 years of age and older: Directly apply 1ml-1.5ml of the product on
sensitive teeth, or use it in a custom mouth tray. Keep your mouth open for 10-15 mins. Then rinse
your month to clean the gel. Use it 1-2 times daily or as recommended by a dentist or physician.
Children under 18 years of age and pregnant, breast feeding women: consult a dentist or
physician prior to use.

INACTIVE INGREDIENT

Carbopol, Deionized Water, Glycerin, Menthol, Sodium Saccharine,SODIUM MONOFLUOROPHOSPHATE